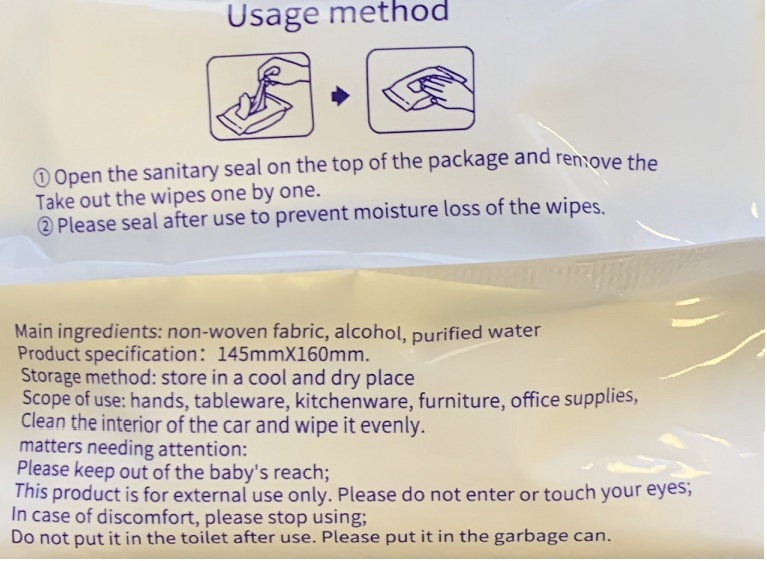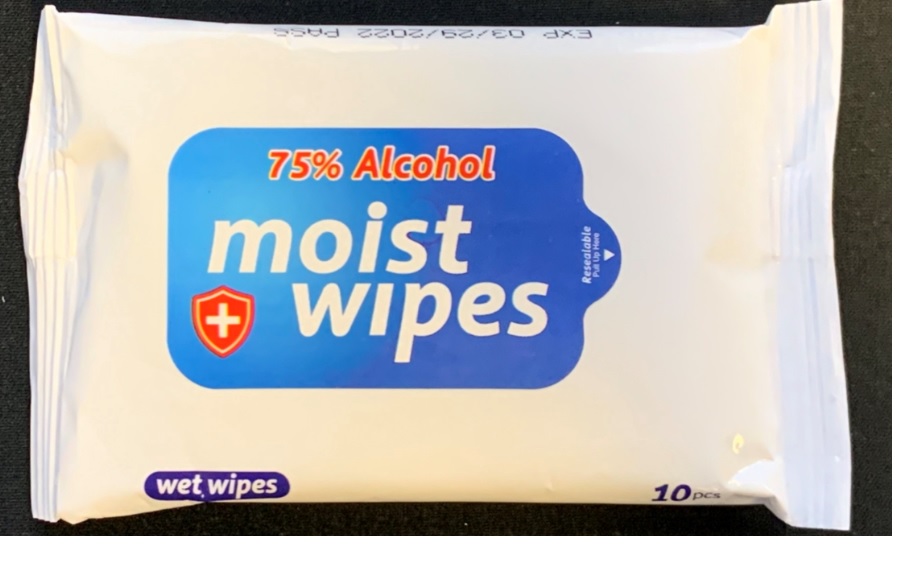 DRUG LABEL: ANTIBACTERIAL WIPES
NDC: 73742-102 | Form: CLOTH
Manufacturer: Golden Applexx Co., Inc.
Category: otc | Type: HUMAN OTC DRUG LABEL
Date: 20220117

ACTIVE INGREDIENTS: ALCOHOL 75 mL/100 mL
INACTIVE INGREDIENTS: WATER

ANTIBACTERIAL WIPES

Active ingredient

Alcohol

Purpose: Antibacterial

INDICATIONS AND USAGE

Scope of use: hands, tableware, kitchenware, furniture, office supplies,

Clean the interior of the car and wipe it evenly.

WARNINGS

matters needing attention:

This product is for external use only. Please do not enter or touch your eyes;

In case of discomfort, please stop using;

Do not put it in the toilet after use. Please put it in the garbage can.

Please keep out of the baby's reach;

Usage method

1 Open the sanitary seal on the top of the package and remove the Take out the wipes one by one.

2 Please seal after use to prevent moisture loss of the wipes.

STORAGE AND HANDLING

Storage method: store in a cool and dry place

INACTIVE INGREDIENT

Main ingredients: non-woven fabric, alcohol, purified water

Product specification: 145mmX160mm.